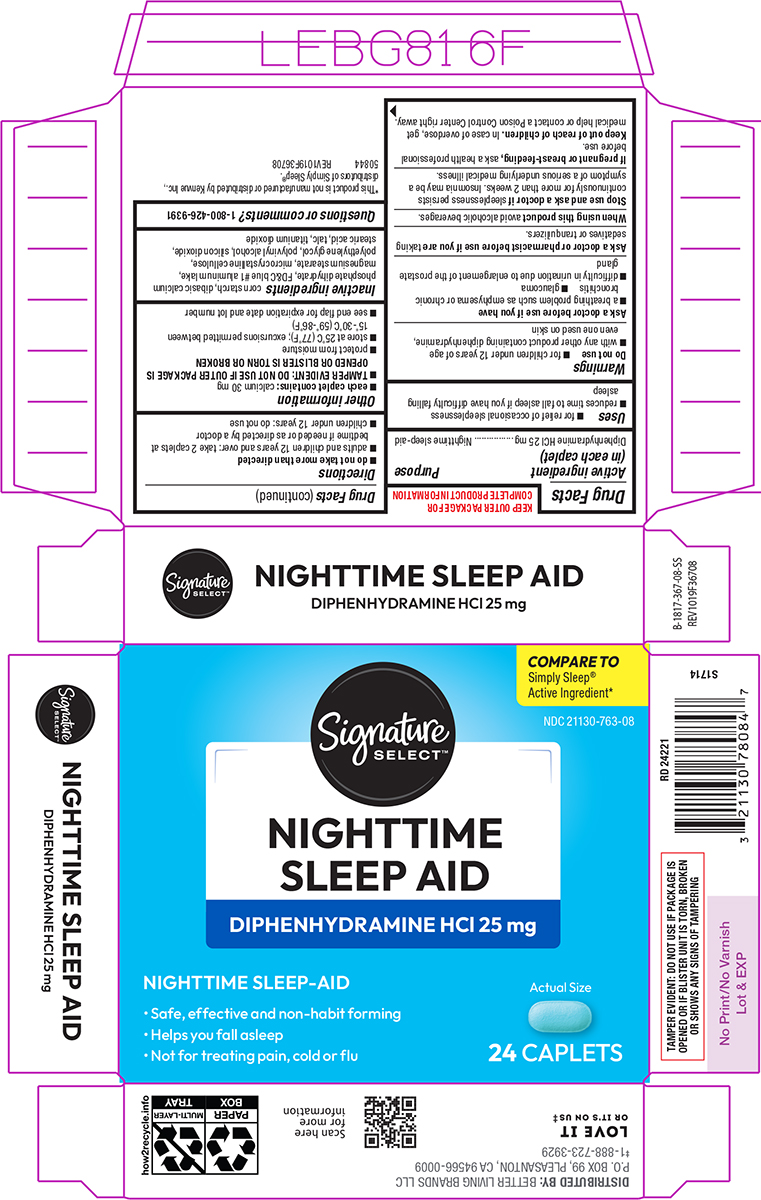 DRUG LABEL: Sleep Aid
NDC: 21130-763 | Form: TABLET, FILM COATED
Manufacturer: Better Living Brands, LLC
Category: otc | Type: HUMAN OTC DRUG LABEL
Date: 20260127

ACTIVE INGREDIENTS: DIPHENHYDRAMINE HYDROCHLORIDE 25 mg/1 1
INACTIVE INGREDIENTS: STARCH, CORN; DIBASIC CALCIUM PHOSPHATE DIHYDRATE; FD&C BLUE NO. 1 ALUMINUM LAKE; MAGNESIUM STEARATE; MICROCRYSTALLINE CELLULOSE; POLYETHYLENE GLYCOL, UNSPECIFIED; POLYVINYL ALCOHOL, UNSPECIFIED; SILICON DIOXIDE; STEARIC ACID; TALC; TITANIUM DIOXIDE

Signature Select 44-367

Active ingredient (in each caplet)

Diphenhydramine HCl 25 mg

Purpose

Nighttime sleep-aid

Uses

- for relief of occasional sleeplessness
- reduces time to fall asleep if you have difficulty falling asleep

Warnings

Do not use

- for children under 12 years of age
- with any other product containing diphenhydramine, even one used on skin

Ask a doctor before use if you have

- a breathing problem such as emphysema or chronic bronchitis
- glaucoma
- difficulty in urination due to enlargement of the prostate gland

Ask a doctor or pharmacist before use if you are

taking sedatives or tranquilizers.

When using this product

avoid alcoholic beverages.

Stop use and ask a doctor if

sleeplessness persists continuously for more than 2 weeks. Insomnia may be a symptom of a serious underlying medical illness.

If pregnant or breast-feeding,

ask a health professional before use.

Keep out of reach of children.

In case of overdose, get medical help or contact a Poison Control Center right away.

Directions

- do not take more than directed
- adults and children 12 years and over: take 2 caplets at bedtime if needed or as directed by a doctor
- children under 12 years: do not use

Other information

- each caplet contains: calcium 30 mg
- TAMPER EVIDENT: DO NOT USE IF OUTER PACKAGE IS OPENED OR BLISTER IS TORN OR BROKEN
- protect from moisture
- store at 25°C (77°F); excursions permitted between 15°-30°C (59°-86°F)
- see end flap for expiration date and lot number

Inactive ingredients

corn starch, dibasic calcium phosphate dihydrate, FD&C blue #1 aluminum lake, magnesium stearate, microcrystalline cellulose, polyethylene glycol, polyvinyl alcohol, silicon dioxide, stearic acid, talc, titanium dioxide

Questions or comments?

1-800-426-9391

Principal Display Panel

Signature
SELECT™

Compare to
Simply Sleep®
active ingredient*

NDC 21130-763-08

NIGHTTIME
SLEEP AID

DIPHENHYDRAMINE HCl 25 mg

NIGHTTIME SLEEP-AID

• Safe, effective and non-habit forming
• Helps you fall asleep
• Not for treating pain, cold or flu

Actual Size

24 CAPLETS

TAMPER EVIDENT: DO NOT USE IF PACKAGE IS
OPENED OR IF BLISTER UNIT IS TORN, BROKEN
OR SHOWS ANY SIGNS OF TAMPERING

*This product is not manufactured or distributed by Kenvue Inc.,
distributors of Simply Sleep®.
50844 REV1019F36708

DISTRIBUTED BY: BETTER LIVING BRANDS LLC
P.O. BOX 99, PLEASANTON, CA 94566-0009
‡1-888-723-3929

LOVE IT
OR IT'S ON US‡

Signature select 44-367